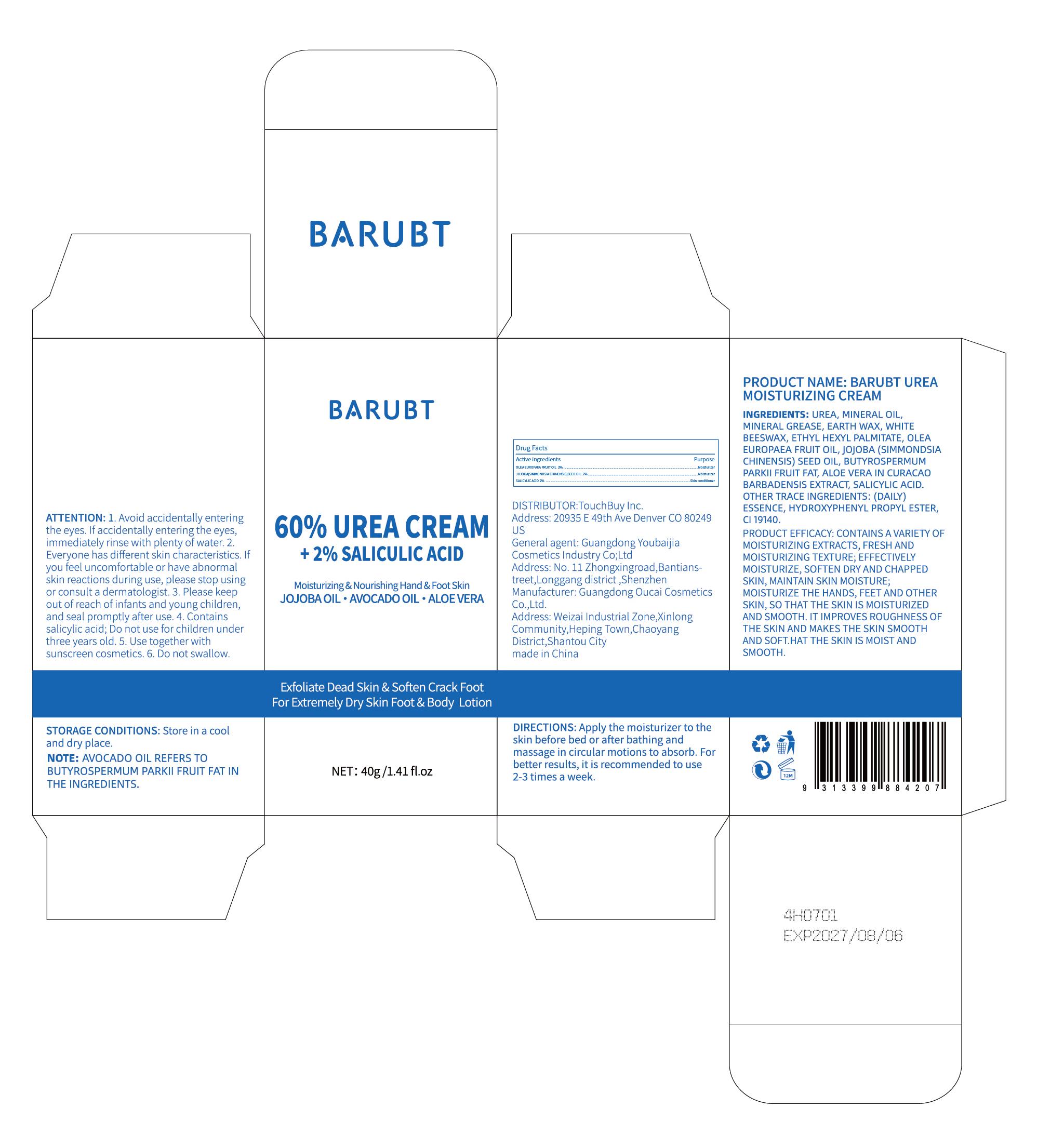 DRUG LABEL: BARUBT Urea Moisturizing Cream
NDC: 84712-022 | Form: CREAM
Manufacturer: Guangdong Youbaijia Cosmetic Industry Co., Ltd
Category: otc | Type: HUMAN OTC DRUG LABEL
Date: 20240918

ACTIVE INGREDIENTS: SALICYLIC ACID 0.8 g/40 g; OLEA EUROPAEA FRUIT VOLATILE OIL 0.8 g/40 g; SIMMONDSIA CHINENSIS SEED 0.8 g/40 g
INACTIVE INGREDIENTS: MINERAL OIL 5.14 g/40 g

ACTIVE INGREDIENT

OLEA EUROPAEA FRUIT OIL 2%
JOJOBA(SIMMONDSIA CHINENSIS)SEED OIL 2%
SALICYLIC ACID 2%

INACTIVE INGREDIENT

UREA, MINERAL OIL,MINERAL GREASE, EARTH WAX, WHITE BEESWAX, ETHYL HEXYL PALMITATE,BUTYROSPERMUM PARKII FRUIT FAT, ALOE VERA IN CURACAO BARBADENSIS EXTRACT, (DAILY)ESSENCE, HYDROXYPHENYL PROPYL ESTER, C1 19140.

Do not use on damaged skin.

Keep away from children. Do not swallow.

PURPOSE

Moisturizing& Nourishing Hand & Foot Skin

QUESTIONS

Contact name: Jessie Peng
Company phone number: +1 818 579 7288
Company e-mail: jessie@registeragentllc.com

STOP USE

lf skin becomes red or irritated, discontinue use immediately and wash with water.

WHEN USING

keep out of eyes. Rinse with water to remove.

WARNINGS

For external use only.

STORAGE AND HANDLING

Keep away from light and in a dry place.

INDICATIONS AND USAGE

CONTAINS A VARIETY OF MOISTURIZING EXTRACTS,FRESH AND MOISTURIZING TEXTURE; EFFECTIVELY MOISTURIZE,SOFTEN DRY AND CHAPPED SKIN, MAINTAIN SKIN MOISTURE; MOISTURIZE THE HANDS, FEET AND OTHER SKIN, SO THAT THE SKIN IS MOISTURIZED AND SMOOTH.IT IMPROVES ROUGHNESS OF THE SKIN AND MAKES THE SKIN SMOOTH AND SOFT.HAT THE SKIN IS MOIST AND SMOOTH.

DOSAGE AND ADMINISTRATION

Apply the moisturizer to the skin before bed or after bathing and massage in circular motions to absorb. For better results, it is recommended to use 2-3 times a week.